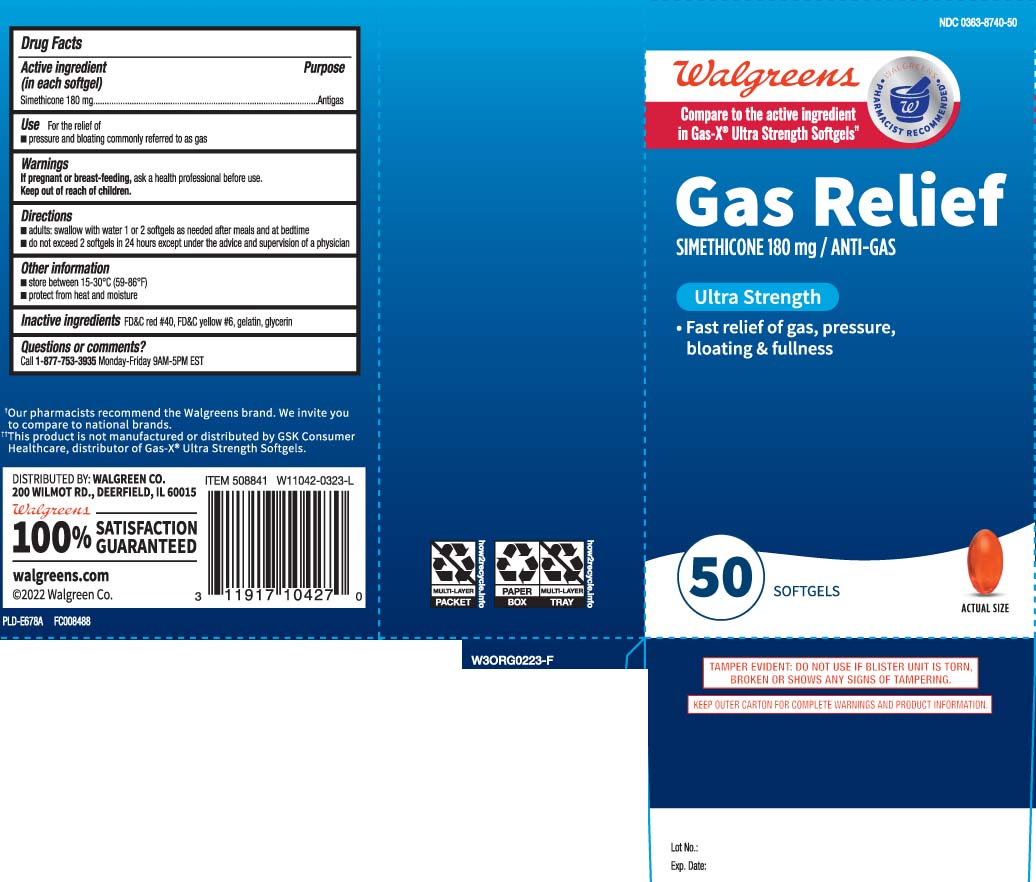 DRUG LABEL: Gas Relief
NDC: 0363-8740 | Form: CAPSULE, LIQUID FILLED
Manufacturer: Walgreens
Category: otc | Type: HUMAN OTC DRUG LABEL
Date: 20240626

ACTIVE INGREDIENTS: DIMETHICONE 180 mg/1 1
INACTIVE INGREDIENTS: FD&C RED NO. 40; FD&C YELLOW NO. 6; GELATIN; GLYCERIN

Drug Facts

Active ingredient (in each softgel)

Simethicone 180 mg

Purpose

Antigas

Uses

For the relief of

- pressure and bloating commonly referred to as gas

Warnings

If pregnant or breast-feeding,

ask a health professional before use.

Directions

- adults: swallow with water 1 or 2 softgels as needed after meals and at bedtime
- do not exceed 2 softgels in 24 hours except under the advice and supervision of a physician

Other information

- store between 15-30°C (59-86°F)
- protect from heat and moisture

Inactive ingredients

FD&C red #40*, FD&C yellow #6, gelatin, glycerin

Questions or comments?

Call 1-877-753-3935 Monday-Friday 9AM-5PM EST

Principal display panel

Compare to the active ingredient in Gas-X® Ultra Strengt Softgels††

Gas Relief

SIMETHICONE 180 mg ANTIGAS

Ultra Strength

SOFTGELS

- For fast relief of pressure, bloating & fullness

††This product is not manufactured or distributed by GSK Consumer Healthcare, distributor of Gas-X® Ultra Strength Softgels.

TAMPER EVIDENT: DO NOT USE IF BLISTER UNIT IS TORN, BROKEN OR SHOWS ANY SIGNS OF TAMPERING.

KEEP OUTER CARTON FOR COMPLETE WARNINGS AND PRODUCT INFORMATION.

DISTRIBUTED BY:WALGREEN CO.

200 WILMOT RD., DEERFIELD, IL 60015

Package Label

WALGREENS Ultra Strength Gas Relief